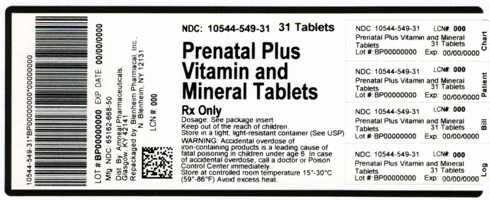 DRUG LABEL: PRENATAL PLUS 
NDC: 10544-549 | Form: TABLET, FILM COATED
Manufacturer: Blenheim Pharmacal, Inc.
Category: prescription | Type: HUMAN PRESCRIPTION DRUG LABEL
Date: 20100908

ACTIVE INGREDIENTS: VITAMIN A ACETATE 3080 [iU]/1 1; BETA CAROTENE 920 [iU]/1 1; ASCORBIC ACID 120 mg/1 1; CHOLECALCIFEROL 400 [iU]/1 1; .ALPHA.-TOCOPHEROL ACETATE, DL- 22 mg/1 1; THIAMINE MONONITRATE 1.84 mg/1 1; RIBOFLAVIN 3 mg/1 1; NIACINAMIDE 20 mg/1 1; PYRIDOXINE HYDROCHLORIDE 10 mg/1 1; FOLIC ACID 1 mg/1 1; CYANOCOBALAMIN 12 ug/1 1; CALCIUM CARBONATE 200 mg/1 1; FERROUS FUMARATE 27 mg/1 1; ZINC OXIDE 25 mg/1 1; CUPRIC OXIDE 2 mg/1 1
INACTIVE INGREDIENTS: ASCORBYL PALMITATE; BUTYLATED HYDROXYTOLUENE; CROSCARMELLOSE SODIUM; DIBASIC CALCIUM PHOSPHATE DIHYDRATE; ALPHA-TOCOPHEROL, DL-; FD&C RED NO. 40; FD&C YELLOW NO. 5; FD&C YELLOW NO. 6; GELATIN; HYPROMELLOSE; MAGNESIUM STEARATE; MALTODEXTRIN; CELLULOSE, MICROCRYSTALLINE; POLYETHYLENE GLYCOL; STARCH, CORN; PROPYLENE GLYCOL; SILICON DIOXIDE; SODIUM ASCORBATE; SODIUM BENZOATE; SORBIC ACID; STEARIC ACID; SUCROSE; SUNFLOWER OIL; TITANIUM DIOXIDE; TRIACETIN

DESCRIPTION

Prenatal Plus Vitamin and Mineral Tablet is an Tan-Yellow colored, modified oval biconvex film coated tablet debossed G12 on one side, and provides 10 vitamins and 4 minerals to supplement the diet before, during and after pregnancy.
Each Prenatal Plus tablet Contains:
Vitamin A (Acetate and Beta Carotene) .......................................4000 I.U.
Vitamin C (Ascorbic acid)……………………………………...........….120 mg
Vitamin D-3 (Cholecalciferol)……………….....................................400 I.U.
Vitamin E (dl- Alpha Tocopheryl Acetate)……………………...............22 mg
Thiamine (Vitamin B-1 from Thiamine Mononitrate………............…1.84 mg
Riboflavin (Vitamin B-2)………………………………………...............…3 mg
Niacin(Niacinamide)…………………………………………………….... 20 mg
Vitamin B-6 (Pyridoxine HCl)…………………………………................10 mg
Folic Acid……………………………………………………............……...1 mg
Vitamin B-12 (Cyanocobalamin)……………………………................12 mcg
Calcium (Calcium Carbonate)……………………………….........…....200 mg
Iron (Ferrous Fumarate)………………………………………...........…...27 mg
Zinc (Zinc Oxide)………………………………………………...........…..25 mg
Copper (Cupric Oxide)…………………………………………...........… ..2 mg
Other ingredients: Ascorbyl Palmitate, Butylated Hydroxytoluene, Croscarmellose sodium, Dicalcium phosphate Dihydrate, DL-alpha-tocopherol, FD&C Blue # 2 lake, FD&C Red # 40, FD&C Red # 40 lake, FD&C yellow # 5, FD&C yellow # 6, FD&C yellow # 6 lake, Gelatin, Hypromellose, Magnesium stearate, Maltodextrin, Microcrystalline Cellulose, Polyethylene Glycol, Pregelatinized corn starch, Propylene Glycol, Silica, Sodium Ascorbate, Sodium Benzoate, Sorbic Acid, Starch, Stearic Acid, Sucrose, SUnflower Oil, Titanium dioxide, Triacetin, Triglycerides.

Indication

To provide Vitamin and Mineral supplementation throughout pregnancy and during the postnatal period for both the lactating and non lactating mother. It is also useful for improving nutritional status prior to conception

Dosage

As a dietary adjunct before, during and after pregnancy, take one tablet daily with a meal, or as directed by a physician.

BOXED WARNING

Warning: Accidental overdose of iron containing products is a leading cause of fatal poisoning in children under age 6. Keep this product out of the reach of children. In case of accidental overdose, call a doctor or poison control center immediately.

Precautions

Folic Acid may partially correct the hematological damage due to vitamin B12 deficiency of pernicious anemia, while the associated neurological damage progresses.

STORAGE AND HANDLING

STORE AT CONTROLLED ROOM TEMPERATURE 15^0 - 30^0C (59^0 - 86^0F). AVOID EXCESS HEAT.

HOW SUPPLIED

Prenatal Plus Vitamin and Mineral Tablet

NDC 65162-668-10: Plastic bottle containing 100 Tablets

NDC 65162-668-50: Plastic bottle containing 500 Tablets

Dispense in a well closed light-resistant container, with a child resistant container.

10544-549-31 - Bottle Label